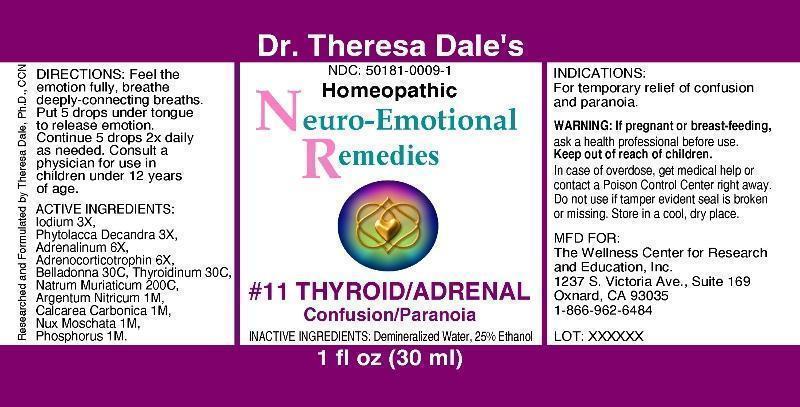 DRUG LABEL: 11 Thyroid Adrenal
NDC: 50181-0009 | Form: LIQUID
Manufacturer: The Wellness Center for Research and Education, Inc.
Category: homeopathic | Type: HUMAN OTC DRUG LABEL
Date: 20250529

ACTIVE INGREDIENTS: IODINE 3 [hp_X]/1 mL; PHYTOLACCA AMERICANA ROOT 3 [hp_X]/1 mL; EPINEPHRINE 6 [hp_X]/1 mL; CORTICOTROPIN 6 [hp_X]/1 mL; SUS SCROFA THYROID 30 [hp_C]/1 mL; SODIUM CHLORIDE 200 [hp_C]/1 mL; SILVER NITRATE 1 [hp_X]/1 mL; OYSTER SHELL CALCIUM CARBONATE, CRUDE 1 [hp_X]/1 mL; NUTMEG 1 [hp_X]/1 mL; PHOSPHORUS 1 [hp_X]/1 mL
INACTIVE INGREDIENTS: WATER; ALCOHOL

Drug Facts

ACTIVE INGREDIENTS:

Iodium 3X, Phytolacca decandra 3X, Adrenalinum 6X, Adrenocorticotrophin 6X, Belladonna 30C, Thyroidinum (suis) 30C, Natrum muriaticum 200C, Argentum nitricum 1X, Calcarea carbonica 1X, Nux moschata 1X, Phosphorus 1X.

INDICATIONS:

For temporary relief of confusion and paranoia.

WARNINGS:

If pregnant or breast-feeding, ask a health professional before use.

Keep out of reach of children. In case of overdose, get medical help or contact a Poison Control Center right away.

Do not use if tamper evident seal is broken or missing.

Store in a cool, dry place.

DIRECTIONS:

Feel the emotion fully, breathe deeply-connecting breaths. Put 5 drops under tongue to release emotion. Continue 5 drops 2x daily as needed. Contult a physician for use in children under 12 years of age.

INACTIVE INGREDIENTS:

Demineralized water, 25% Ethanol.

KEEP OUT OF REACH OF CHILDREN.

In case of overdose, get medical help or contact a Poison Control Center right away.

INDICATIONS:

For temporary relief of confusion and paranoia.

QUESTIONS:

MFD. FOR:

The Wellness Center for

Research and Education, Inc.

1237 S. victoria Ave., Ste 169

Oxnard, CA 93035

1-866-962-6484

PACKAGE LABEL DISPLAY

Dr. Theresa Dale's

NDC 50181-0009-1

Homeopathic

Neuro Emotional Remedies

11 THYROID ADRENAL

Confusion paranoia

1 fl oz (30 ml)